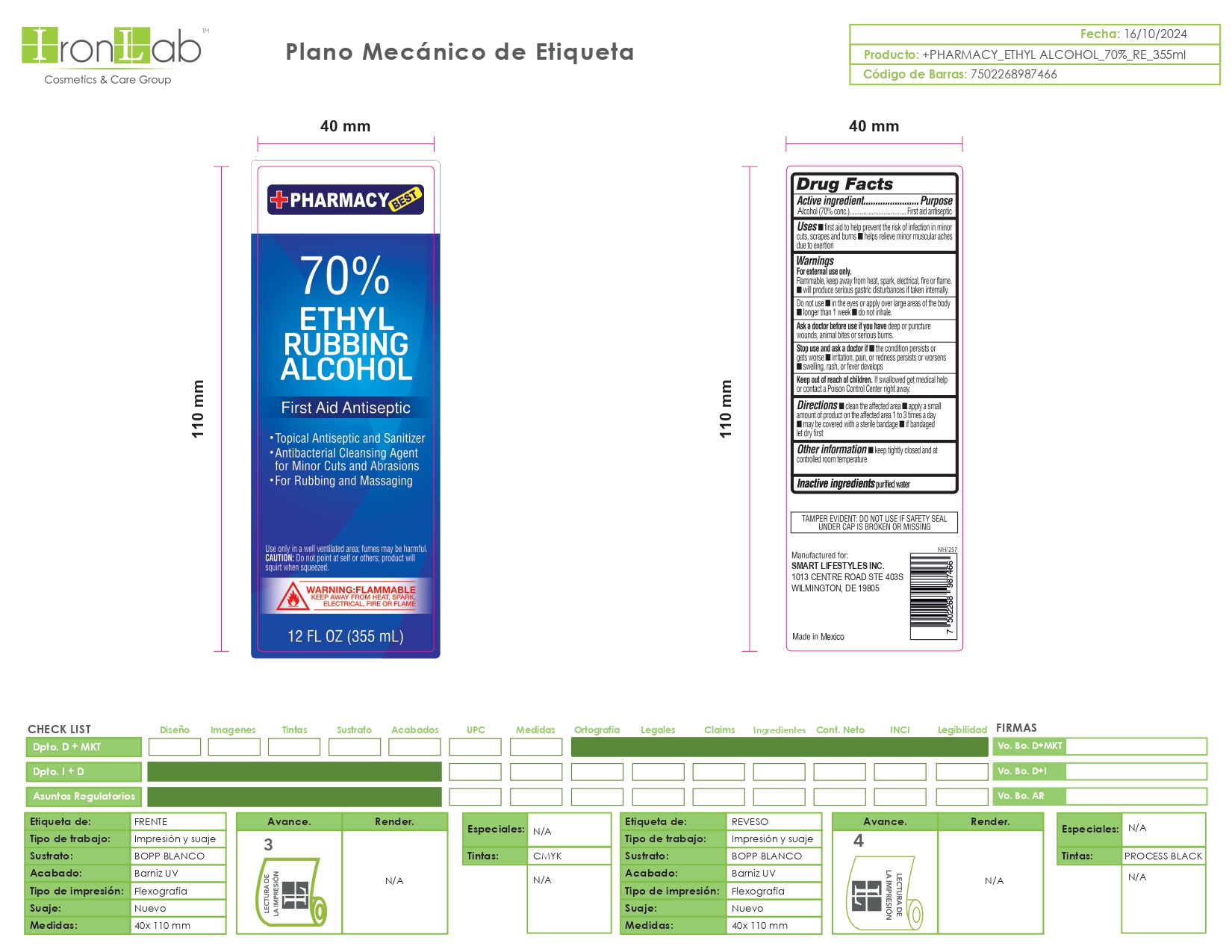 DRUG LABEL: 70 Rubbing Ethyl Alcohol
NDC: 74375-050 | Form: LIQUID
Manufacturer: Iron Lab SA de CV
Category: otc | Type: HUMAN OTC DRUG LABEL
Date: 20260217

ACTIVE INGREDIENTS: ALCOHOL 70 mL/100 mL
INACTIVE INGREDIENTS: WATER

70 Rubbing Alcohol Iron Lab SA de CV

INDICATIONS AND USAGE

To decrease bacteria on the skin that could cause disease. Recommended for repeated use.

ACTIVE INGREDIENT

70 Ethyl Alcohol

DOSAGE AND ADMINISTRATION

Thoroughly cover your hands with product and allow to dry without wiping. Children under 6 years of age should be supervised when using this product. Not recommended for infants.

WARNINGS

For external use only: hands. Flammable, Keep away from fire of flame.

KEEP OUT OF REACH OF CHILDREN

If swallowed, get medical help or contact a Poison Control Center right away

ASK DOCTOR

Irritation or redness develops. Condition persist for more than 72 hours.

INACTIVE INGREDIENT

Purified Water

ACTIVE INGREDIENT

70% Ethyl Alcohol

STOP USE

Keep out of eyes. In case of contact with eyes, flush thoroughly with water. Avoid contact with broken skin. Do not inhale or ingest.

PURPOSE

Antiseptic Alcohol

PACKAGE LABEL

70 Rubbing Alcohol